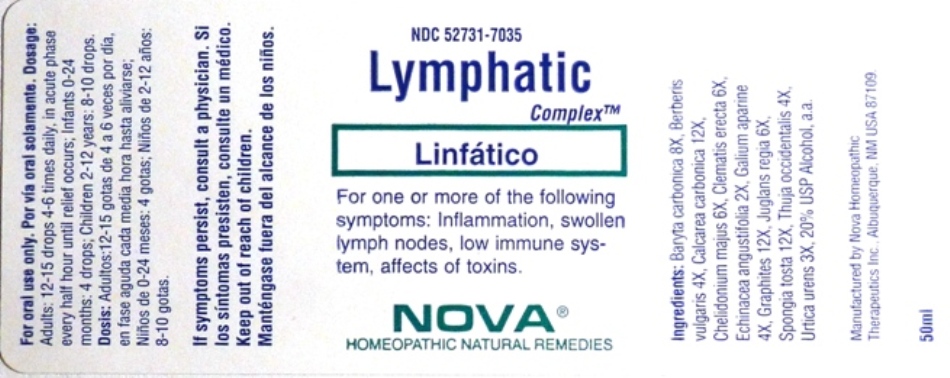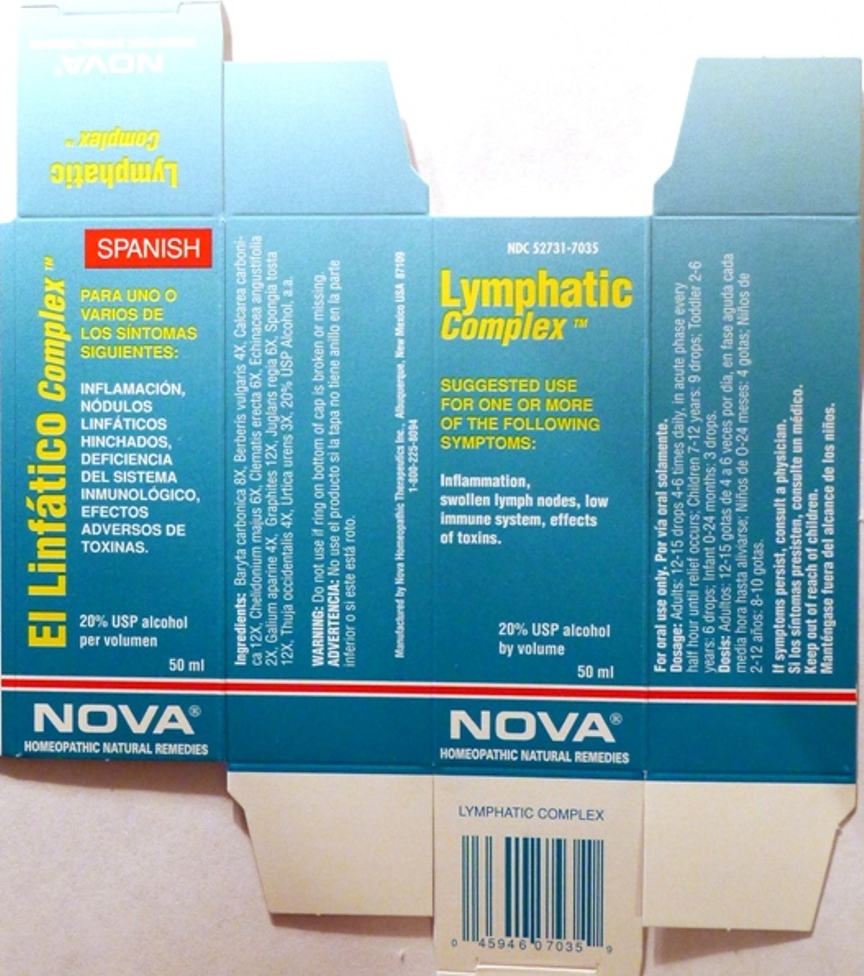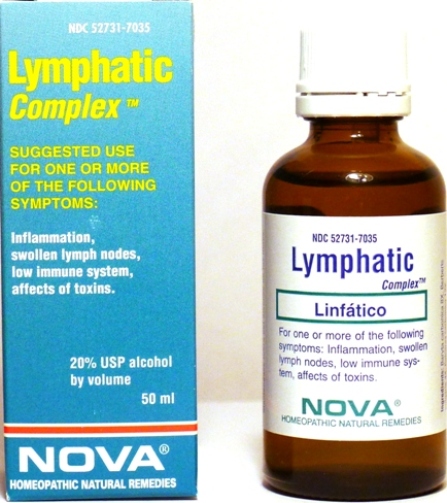 DRUG LABEL: Lymphatic Complex
NDC: 52731-7035 | Form: LIQUID
Manufacturer: Nova Homeopathic Therapeutics, Inc.
Category: homeopathic | Type: HUMAN OTC DRUG LABEL
Date: 20110601

ACTIVE INGREDIENTS: BARIUM CARBONATE 8 [hp_X]/1 mL; BERBERIS VULGARIS ROOT BARK 4 [hp_X]/1 mL; OYSTER SHELL CALCIUM CARBONATE, CRUDE 12 [hp_X]/1 mL; CHELIDONIUM MAJUS 6 [hp_X]/1 mL; CLEMATIS RECTA FLOWERING TOP 6 [hp_X]/1 mL; ECHINACEA ANGUSTIFOLIA 2 [hp_X]/1 mL; GALIUM APARINE 4 [hp_X]/1 mL; GRAPHITE 12 [hp_X]/1 mL; JUGLANS REGIA FRUIT RIND, IMMATURE 6 [hp_X]/1 mL; SPONGIA OFFICINALIS SKELETON, ROASTED 12 [hp_X]/1 mL; THUJA OCCIDENTALIS LEAFY TWIG 4 [hp_X]/1 mL; URTICA URENS 3 [hp_X]/1 mL
INACTIVE INGREDIENTS: ALCOHOL

Lymphatic Complex

Purpose:

Suggested use for one or more of the following symptoms:

Inflammation,swollen lymph nodes, low immune system, effects of toxins.

Usage and Dosage:

For oral use only.

DOSAGE AND ADMINISTRATION

Adults:
In Acute Phase:
12-15 drops, every half hour until relief occurs
When Relief Occurs:
12-15 drops, 4-6 times per day
Children 2-12 years:
8-10 drops, 4-6 times per day

Infants 0-24 months:
4 drops, 4-6 times per day

Warnings:

Keep out of reach of children.

WARNINGS

If symptoms persist, consult a physician.

Do not use if ring on bottom of cap is broken or missing.

Active Ingredients:

Baryta carbonica 8X, Berberis vulgaris 4X, Calcarea carbonica 12X, Chelidonium majus 6X, Clematis erecta 6X, Echinacea angustifolia 2X, Galium aparine 4X, Graphites 12X, Juglans regia 6X, Spongia tosta
12X, Thuja occidentalis 4X, Urtica urens 3X

Inactive Ingredients:

Alcohol, 20% USP

QUESTIONS

Manufactured by Nova Homeopathic Therapeutics Inc., Albuquerque, New Mexico USA 87109
1-800-225-8094

PACKAGE LABEL

Lymphatic Complex Product

Lymphatic Complex Bottle Label

Lymphatic Complex Box